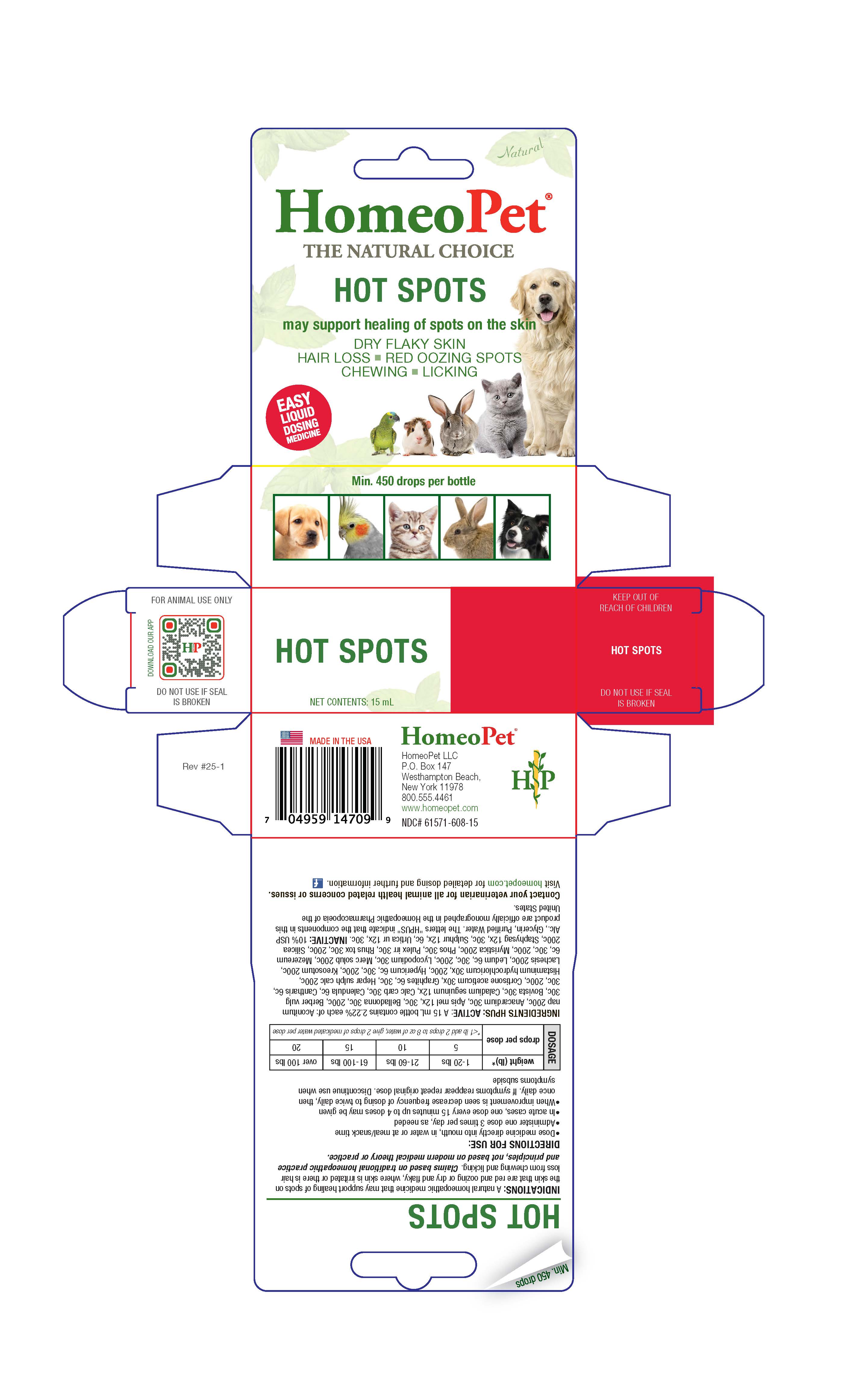 DRUG LABEL: Hot Spots
NDC: 61571-608 | Form: LIQUID
Manufacturer: HomeoPet, LLC
Category: homeopathic | Type: OTC ANIMAL DRUG LABEL
Date: 20251211

ACTIVE INGREDIENTS: ACONITUM NAPELLUS WHOLE 200 [hp_C]/15 mL; SEMECARPUS ANACARDIUM FRUIT 30 [hp_C]/15 mL; APIS MELLIFERA 12 [hp_X]/15 mL; ATROPA BELLADONNA 30 [hp_C]/15 mL; BERBERIS VULGARIS ROOT BARK 30 [hp_C]/15 mL; LYCOPERDON UTRIFORME FRUITING BODY 30 [hp_C]/15 mL; DIEFFENBACHIA SEGUINE WHOLE 12 [hp_X]/15 mL; OYSTER SHELL CALCIUM CARBONATE, CRUDE 30 [hp_C]/15 mL; CALENDULA OFFICINALIS FLOWERING TOP 6 [hp_C]/15 mL; LYTTA VESICATORIA 6 [hp_C]/15 mL; CORTISONE ACETATE 30 [hp_X]/15 mL; GRAPHITE 6 [hp_C]/15 mL; CALCIUM SULFIDE 200 [hp_C]/15 mL; HISTAMINE DIHYDROCHLORIDE 30 [hp_X]/15 mL; HYPERICUM PERFORATUM WHOLE 6 [hp_C]/15 mL; WOOD CREOSOTE 200 [hp_C]/15 mL; LACHESIS MUTA VENOM 200 [hp_C]/15 mL; RHODODENDRON TOMENTOSUM LEAFY TWIG 6 [hp_C]/15 mL; LYCOPODIUM CLAVATUM SPORE 30 [hp_C]/15 mL; MERCURIUS SOLUBILIS 200 [hp_C]/15 mL; DAPHNE MEZEREUM BARK 6 [hp_C]/15 mL; VIROLA SEBIFERA RESIN 200 [hp_C]/15 mL; PHOSPHORUS 30 [hp_C]/15 mL; PULEX IRRITANS WHOLE 30 [hp_C]/15 mL; TOXICODENDRON PUBESCENS LEAF 30 [hp_C]/15 mL; SILICON DIOXIDE 200 [hp_C]/15 mL; STAPHISAGRIA MACROSPERMA SEED 12 [hp_X]/15 mL; SULFUR 12 [hp_X]/15 mL; URTICA URENS WHOLE 12 [hp_X]/15 mL
INACTIVE INGREDIENTS: WATER; ALCOHOL; GLYCERIN

Hot Spots

Hot Spots

May support healing of spots on the skin

HOT SPOTS-DRY FLAKING SPOTS

HAIR LOSS-RED OOZING SPOTS

CHEWING-LICKING

Directions for Use and Dosage

- Dose remedy directly into mouth, in water or at meal/snack time
- Administer one dose 3 times per day, as needed
- In acute cases, one dose every 15 minutes up to 4 doses may be given
- When improvement is seen decrease frequency of dosing to twice daily, then once daily. If symptoms reappear repeat original dose. Discontinue use when symptoms subside

DOSAGE | weight (lb)* | 1-20 lbs | 21-60 lbs | 61-100 lbs | over 100 lbs
DOSAGE | drops per dose | 5 | 10 | 15 | 20
DOSAGE | drops per dose | *< 1 lb add 2 drops to 8 oz of water, give 2 drops of medicated water per dose

Contact Veterinarian

Contact your veterinarian for all animal health related concerns or issues.

Visit homeopet.com for detailed dosing and further information.

Ingredients HPUS: Active

Aconitum nap 200c, Anacardium 30c, Apis mel 12x, 30c, Belladonna 30c, 200c, Berberis vulg 30c, Bovista 30c, Caladium seguinum 12x, Calc carb 30c, Calendula 6c, Cantharis 6c, 30c, 200c, Cortisone aceticum 30x, Graphites 6c, 30c, Hepar sulph calc 200c, Histaminum hydrochloricum 30x, 200c, Hypericum 6c, 30c, 200c, Kreosotum 200c, Lachesis 200c, Ledum 6c, 30c, 200c, Lycopodium 30c, Merc solub 200c, Mezereum 6c, 30c, 200c, Myristica 200c, Phos 30c, Pulex irr 30c, Rhus tox 30c, 200c, Silicea 200c, Staphysag 12x, 30c, Sulphur 12x, 6c, Urtica ur 12x, 30c.

Inactive Ingredients

USP Alcohol, Glycerin, Purified Water

Indications

A natural homeopathic medicine that may support healing of spots on the skin that are red and oozing or dry and flaky, where skin is irrirated or there is hair loss from chewing and licking. Claims based on traditional homeopathic practice and principles, not based on modern medical theory or practice.